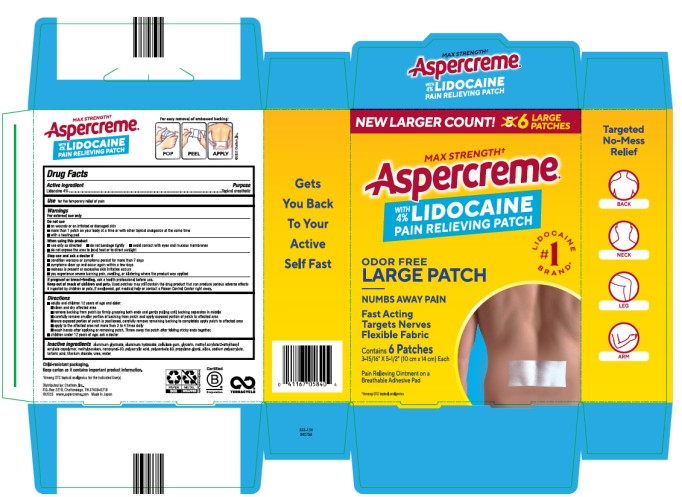 DRUG LABEL: Aspercreme with Lidocaine
NDC: 41167-0584 | Form: PATCH
Manufacturer: Chattem, Inc.
Category: otc | Type: HUMAN OTC DRUG LABEL
Date: 20260119

ACTIVE INGREDIENTS: LIDOCAINE 4 g/100 g
INACTIVE INGREDIENTS: ALUMINUM GLYCINATE; ALUMINUM HYDROXIDE; CELLULOSE GUM; GLYCERIN; METHYLPARABEN; NONOXYNOL-30; POLYACRYLIC ACID (250000 MW); POLYSORBATE 80; PROPYLENE GLYCOL; SILICON DIOXIDE; SODIUM POLYACRYLATE (8000 MW); TARTARIC ACID; TITANIUM DIOXIDE; UREA; WATER

Aspercreme Lidocaine Patch

Active ingredient

Lidocaine 4%

Purpose

Topical anesthetic

Use

for the temporary relief of pain

Warnings

For external use only

Do not use

■ on wounds or on irritated or damaged skin

■ more than 1 patch on your body at a time or with other topical analgesics at the same time

■ with a heating pad

When using this product

■ use only as directed

■ do not bandage tightly

■ avoid contact with eyes and mucous membranes

■ do not expose the area to local heat or to direct sunlight

Stop use and ask a doctor if

■ condition worsens or symptoms persist for more than 7 days

■ symptoms clear up and occur again within a few days

■ redness is present or excessive skin irritation occurs

■ you experience severe burning pain, swelling, or blistering where the product was applied

If pregnant or breast-feeding,

ask a health professional before use.

Keep out of reach of children and pets.

Used patches may still contain the drug product that can produce serious adverse effects if ingested by children or pets. If swallowed, get medical help or contact a Poison Control Center right away.

Directions

■ adults and children 12 years of age and older:

■ clean and dry affected area

■ remove backing from patch by firmly grasping both ends and gently pulling until backing separates in middle

■ carefully remove smaller portion of backing from patch and apply exposed portion of patch to affected area

■ once exposed portion of patch is positioned, carefully remove remaining backing to completely apply patch to affected area

■ apply to the affected area not more than 3 to 4 times daily

■ wash hands after applying or removing patch. Throw away the patch after folding sticky ends together.

■ children under 12 years of age: ask a doctor

Inactive ingredients

aluminum glycinate, aluminum hydroxide, cellulose gum, glycerin, methyl acrylate/2-ethylhexyl acrylate copolymer, methylparaben, nonoxynol-30, polyacrylic acid, polysorbate 80, propylene glycol, silica, sodium polyacrylate, tartaric acid, titanium dioxide, urea, water

PRINCIPAL DISPLAY PANEL

Aspercreme
with 4% Lidocaine
PAIN RELIEVING PATCH